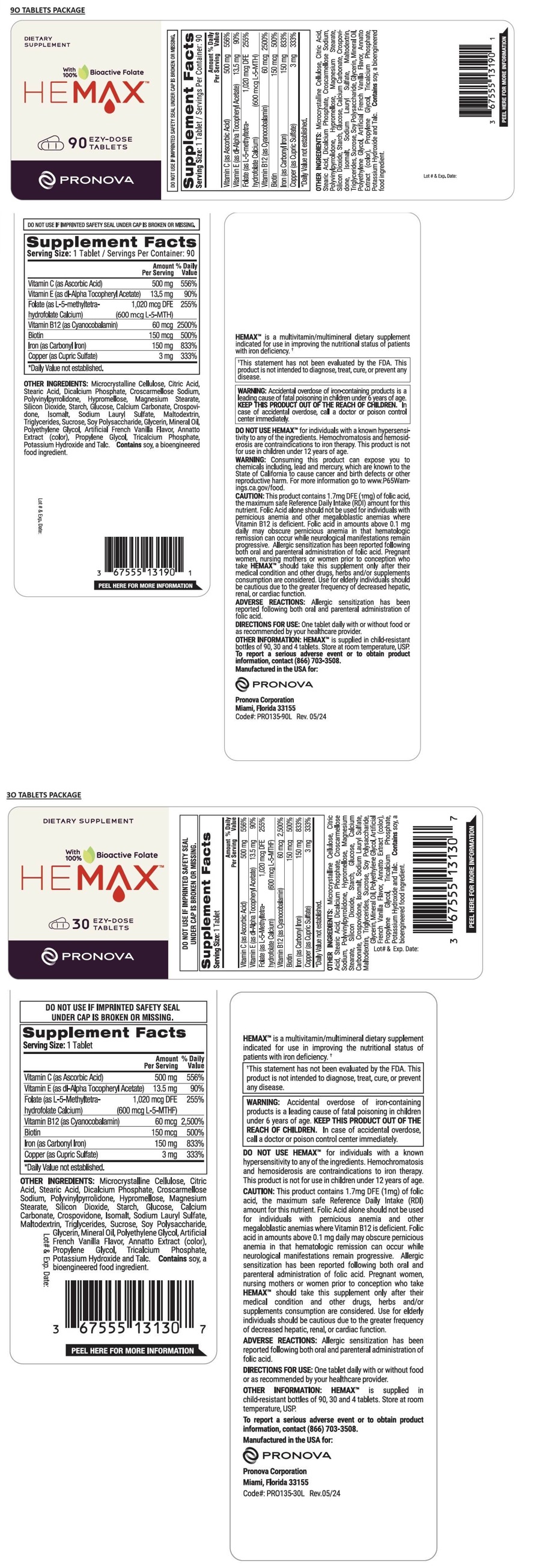 DRUG LABEL: HEMAX
NDC: 67555-131 | Form: TABLET
Manufacturer: Pronova Corporation
Category: other | Type: DIETARY SUPPLEMENT
Date: 20240807

ACTIVE INGREDIENTS: ASCORBIC ACID 500 mg/1 1; .ALPHA.-TOCOPHEROL ACETATE, DL- 13.5 mg/1 1; LEVOMEFOLATE CALCIUM 600 ug/1 1; CYANOCOBALAMIN 60 ug/1 1; BIOTIN 150 ug/1 1; IRON 150 mg/1 1; CUPRIC SULFATE 3 mg/1 1
INACTIVE INGREDIENTS: MICROCRYSTALLINE CELLULOSE; CITRIC ACID MONOHYDRATE; STEARIC ACID; ANHYDROUS DIBASIC CALCIUM PHOSPHATE; CROSCARMELLOSE SODIUM; POVIDONE, UNSPECIFIED; HYPROMELLOSE, UNSPECIFIED; MAGNESIUM STEARATE; SILICON DIOXIDE; STARCH, RICE; ANHYDROUS DEXTROSE; CALCIUM CARBONATE; CROSPOVIDONE, UNSPECIFIED; ISOMALT; SODIUM LAURYL SULFATE; MALTODEXTRIN; MEDIUM-CHAIN TRIGLYCERIDES; SUCROSE; SOYBEAN COTYLEDON CELL WALL POLYSACCHARIDES; GLYCERIN; MINERAL OIL; POLYETHYLENE GLYCOL, UNSPECIFIED; ANNATTO; PROPYLENE GLYCOL; TRICALCIUM PHOSPHATE; POTASSIUM HYDROXIDE; TALC

HEMAX™

STATEMENT OF IDENTITY

Supplement Facts
Serving Size: 1 Tablet / Servings Per Container: 90
 | Amount | % Daily
 | Per Serving | Value
Vitamin C (as Ascorbic Acid) | 500 mg | 556%
Vitamin E (as dl-Alpha Tocopheryl Acetate) | 13.5 mg | 90%
Folate (as L-5-methyltetrahydrofolate Calcium) | 1,020 mcg DFE | 255%
 | (600 mcg L-5-MTH)
Vitamin B12 (as Cyanocobalamin) | 60 mcg | 2,500%
Biotin | 150 mcg | 500%
Iron (as Carbonyl Iron) | 150 mg | 833%
Copper (as Cupric Sulfate) | 3 mg | 333%
*Daily Value not established

OTHER INGREDIENTS: Microcrystalline Cellulose, Citric Acid, Stearic Acid, Dicalcium Phosphate, Croscarmellose Sodium, Polyvinylpyrrolidone, Hypromellose, Magnesium Stearate, Silicon Dioxide, Starch, Glucose, Calcium Carbonate, Crospovidone, Isomalt, Sodium Lauryl Sulfate, Maltodextrin, Triglycerides, Sucrose, Soy Polysaccharide, Glycerin, Mineral Oil, Polyethylene Glycol, Artificial French Vanilla Flavor, Annatto Extract (color), Propylene Glycol, Tricalcium Phosphate, Potassium Hydroxide and Talc. Contains soy, a bioengineered food ingredient.

HEMAXTM is a multivitamin/multimineral dietary supplement indicated for use in improving the nutritional status of patients with iron deficiency.†

†This statement has not been evaluated by the FDA. This product is not intended to diagnose, treat, cure, or prevent any disease.

WARNINGS

WARNING Accidental overdose of iron-containing products is a leading cause of fatal poisoning in children under 6 years of age. KEEP THIS PRODUCT OUT OF THE REACH OF CHILDREN. In case of accidental overdose, call a doctor or poison control center immediately.

DO NOT USE HEMAXTM for individuals with a known hypersensitivity to any of the ingredients. Hemochromatosis and hemosiderosis are contraindications to iron therapy. This product is not for use in children under 12 years of age.

WARNING:

Consuming this product can expose you to chemicals including, lead and mercury, which are known to the State of California to cause cancer and birth defects or other reproductive harm. For more information go to www.P65Warnings.ca.gov/food.

CAUTION:

This product contains 1.7mg DFE (1mg) of folic acid, the maximum safe Reference Daily Intake (RDI) amount for this nutrient. Folic Acid alone should not be used for individuals with pernicious anemia and other megaloblastic anemias where Vitamin B12 is deficient. Folic acid in amounts above 0.1 mg daily may obscure pernicious anemia in that hematologic remission can occur while neurological manifestations remain progressive. Allergic sensitization has been reported following both oral and parenteral administration of folic acid. Pregnant women, nursing mothers or women prior to conception who take HEMAXTM should take this supplement only after their medical condition and other drugs, herbs and/or supplements consumption are considered. Use for elderly individuals should be cautious due to the greater frequency of decreased hepatic, renal, or cardiac function.

ADVERSE REACTIONS:

Allergic sensitization has been reported following both oral and parenteral administration of folic acid.

DIRECTIONS FOR USE:

One tablet daily with or without food or as recommended by your healthcare provider.

OTHER INFORMATION:

HEMAXTM is supplied in child-resistant bottles of 90, 30 and 4 tablets. Store at room temperature, USP.

To report a serious adverse event or to obtain product information, contact (866) 703-3508.

Manufactured in the USA for:

Pronova Corporation
Miami, Florida 33155

HEALTH CLAIM

DIETARY SUPPLEMENT

With 100% Bioactive Folate

EZY-DOSE TABLETS

DO NOT USE IF IMPRINTED SAFETY SEAL UNDER CAP IS BROKEN OR MISSING.